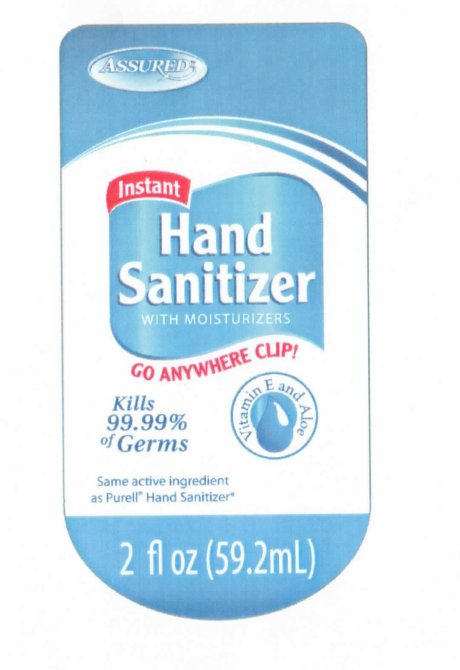 DRUG LABEL: Assured Hand Sanitizer With Moisturizers
NDC: 33992-1080 | Form: GEL
Manufacturer: Greenbrier International, Inc
Category: otc | Type: HUMAN OTC DRUG LABEL
Date: 20100506

ACTIVE INGREDIENTS: ALCOHOL 62 mL/100 mL
INACTIVE INGREDIENTS: WATER; TROLAMINE; GLYCERIN; PROPYLENE GLYCOL

Assured Instant Hand Sanitizer With Moisturizers

ACTIVE INGREDIENT

Active Ingredients............................................................Purpose
Ethyl Alcohol 62 percent.................................................Antiseptic

PURPOSE

Uses: Helps decrease bacteria on skin. Recommended for repeated use.

Warnings
For external use only.
Flammable. Keep away from fire or flame. Do not apply around eyes.

When using this product, avoid contact with eyes. In case of contact flush eyes with water.

Stop use and ask a doctor if redness or irritation develop and persist for more than 72 hrs.

Keep out of reach of children. Children must be supervised in use of this product.

DOSAGE AND ADMINISTRATION

Directions: Pump as needed into your palms and thoroughly spread on both hands.

Other information: Store at 20 C 68 to 77 F. May discolor fabrics.

INACTIVE INGREDIENT

Inactive Ingredients: Water, triethanolamine, glycerin, propylene glycol, tocopheryl acetate, aloe barbadensis gel, carbomer, fragrance.

PACKAGE LABEL

Assured

Instant Hand Sanitizer with Moisturizers

Go Anywhere Clip!

Kills 99.99 percent of Germs

Vitamin e and aloe vera

Same active ingredient as Purell Hand Sanitizer

2fl oz 59.2mL